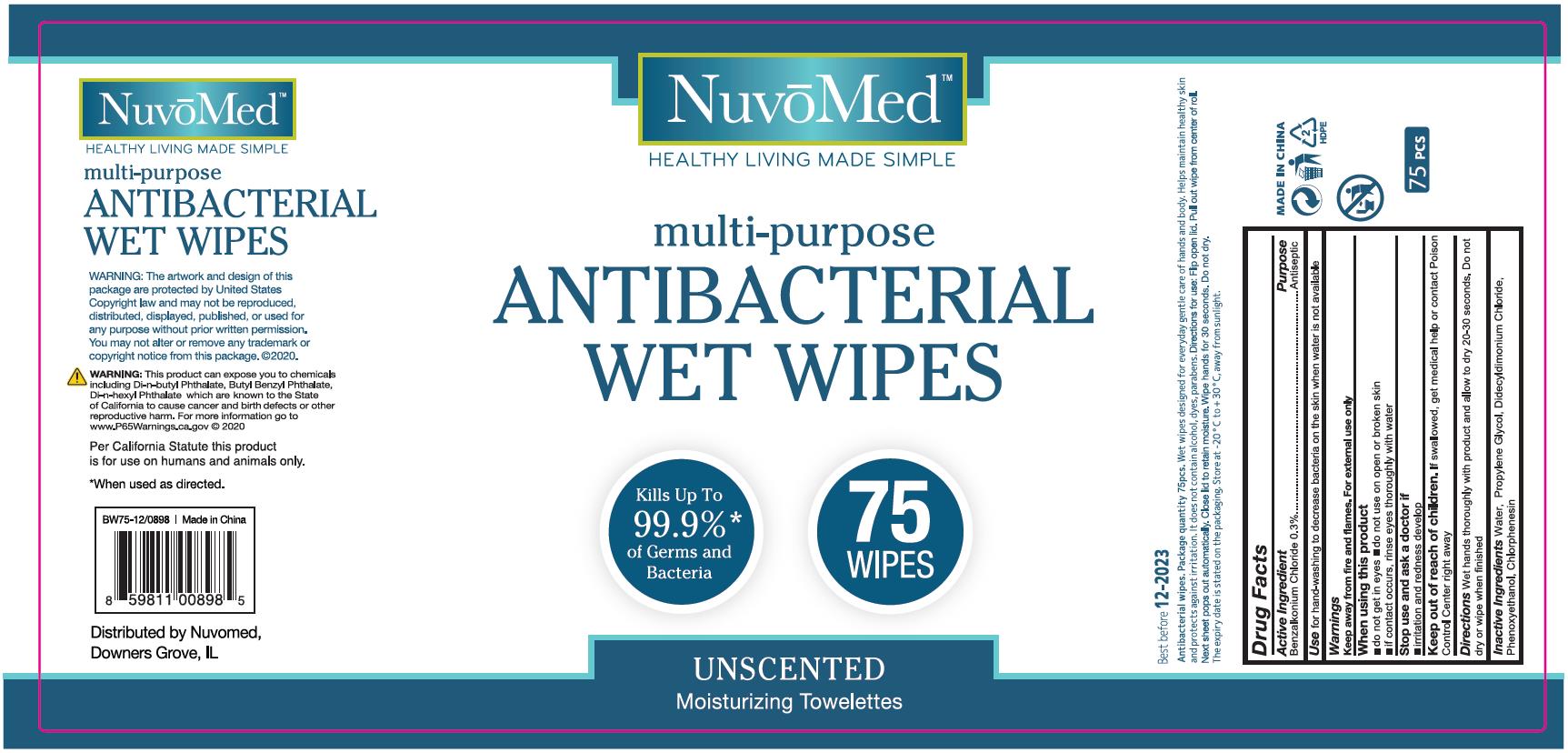 DRUG LABEL: NuvoMed multi-purpose ANTIBACTERIAL WET WIPES
NDC: 78356-231 | Form: CLOTH
Manufacturer: Zhejiang Yiwu Anrou Sanitation Article Co., Ltd
Category: otc | Type: HUMAN OTC DRUG LABEL
Date: 20200919

ACTIVE INGREDIENTS: BENZALKONIUM CHLORIDE 11 mg/1 1
INACTIVE INGREDIENTS: PROPYLENE GLYCOL; WATER; DIDECYLDIMONIUM CHLORIDE; CHLORPHENESIN; PHENOXYETHANOL

Anrou-Nuvomed, Antibacterial Wet Wipes, Benzalkonium Chloride 0.3%

Active Ingredient

Benzalkonium Chloride 0.3% w/w ...... Purpose: Antiseptic

Purpose

Antiseptic

Use

for hand-washing to decrease bacteria on the skin when water is not available

Warnings

Keep away from fire and flames. For external use only

When using this product

- do not get in eyes
- if contact occurs,rinse eyes thoroughly with water

- do not use on open or broken skin

Stop use and ask a doctor if

- irritation and redness develop

Keep out of reach of children.

If swallowed, get medical help or contact Poison Control Center right away.

Directions

Wet hands thoroughly with product and allow to dry 20-30 seconds. Do not dry or wipe when finished.

STORAGE AND HANDLING

Directions for use: Flip open lid. Pull out wipe from center of roll. Next sheet pops out automatically. Close lid to remain moisture. Wipe hands for 30 seconds. Do not dry.

The expiry date is stated on the packaging. Store at -20℃ to +30℃, away from sunlight.

Inactive Ingredients

Water, Propylene Glycol, Didecyldimonium Chloride, Phenoxyethanol, Chlorphenesin